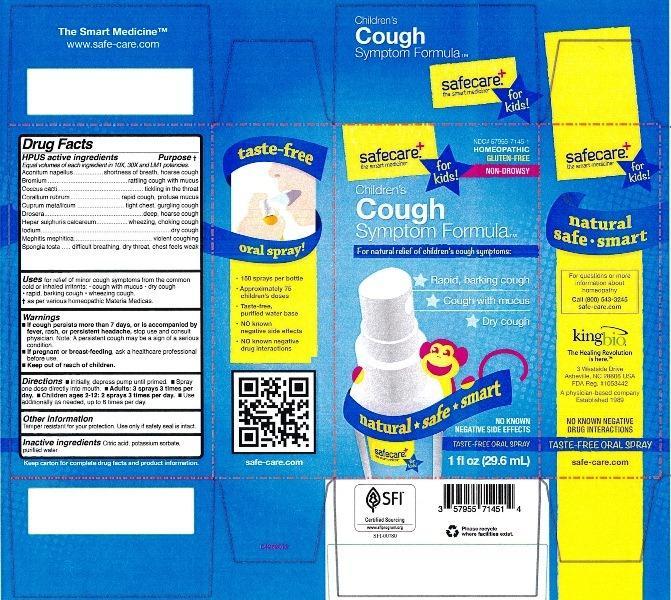 DRUG LABEL: Childrens Cough Symptom Formula
NDC: 57955-7145 | Form: LIQUID
Manufacturer: King Bio Inc.
Category: homeopathic | Type: HUMAN OTC DRUG LABEL
Date: 20130214

ACTIVE INGREDIENTS: ACONITUM NAPELLUS 10 [hp_X]/29.6 mL; BROMINE 10 [hp_X]/29.6 mL; PROTORTONIA CACTI 10 [hp_X]/29.6 mL; CORALLIUM RUBRUM EXOSKELETON 10 [hp_X]/29.6 mL; COPPER 10 [hp_X]/29.6 mL; DROSERA ROTUNDIFOLIA 10 [hp_X]/29.6 mL; CALCIUM SULFIDE 10 [hp_X]/29.6 mL; IODINE 10 [hp_X]/29.6 mL; MEPHITIS MEPHITIS ANAL GLAND FLUID 10 [hp_X]/29.6 mL; SPONGIA OFFICINALIS SKELETON, ROASTED 10 [hp_X]/29.6 mL
INACTIVE INGREDIENTS: CITRIC ACID MONOHYDRATE; POTASSIUM SORBATE; WATER

Childrens Cough Symptom Formula

Active Ingredients

HPUS active ingredients

Equal volumes of each ingredient in 10X, 30X and LM1 potencies.

Aconitum napellus, Bromium, Coccus cacti, Corallium rubrum, Cuprum metallicum, Drosera, Hepar sulphuris calcareum, Iodium, Mephitis mephitica and Spongia tosta

Inactive Ingredient

Citric acid, potassium sorbate and purified water

Purpose

HPUS active ingredients Purpose†

Equal volumes of each ingredient in 10X, 30X and LM1 Potencies.

Aconitum napellus.........................................................shortness of breath, hoarse cough

Bromium........................................................................rattling cough with mucus

Coccus cacti...................................................................tickling in the throat

Corallium rubrum...........................................................rapid cough, profuse mucus

Cuprum metallicum........................................................tight chest, gurgling cough

Drosera.........................................................................deep, hoarse cough

Hepar sulphuris calcareum..............................................wheezing, choking cough

Iodium...........................................................................dry cough

Mephitis mephitica.........................................................violent coughing

Spongia tosta................................................................difficult breathing, dry throat, chest feels weak

Warnings

- If cough persists more than 7 days, or is accompanied by fever, rash, or persistent headache, stop use and consult physician. Note: A persistent cough may be a sign of a serious condition.
- If pregnant or breast-feeding, ask a healthcare professional before use.
- Keep out of reach of children.

Other information: Tamper resistant for your protection. Use only if safety seal is intact.

Keep out of reach of children

Directions

- Initially, depress pump until primed.
- Spray one dose directly into mouth.
- Adults: 3 sprays 3 times per day.
- Children ages 2-12: 2 sprays 3 times per day.
- Use additionally as needed, up to 6 times per day.

INDICATIONS AND USAGE

Uses for relief of minor cough symptoms from the common cold or inhaled irritants:

- cough with mucus
- dry cough
- rapid, barking cough
- wheezing cough

† as per the various homeopathic Materia Medicas.

PACKAGE LABEL

King Bio Inc.

3 Westside Drive

Asheville, NC 28806

For questions or more information about homeopathy call (800) 543-3245 or safe-care.com